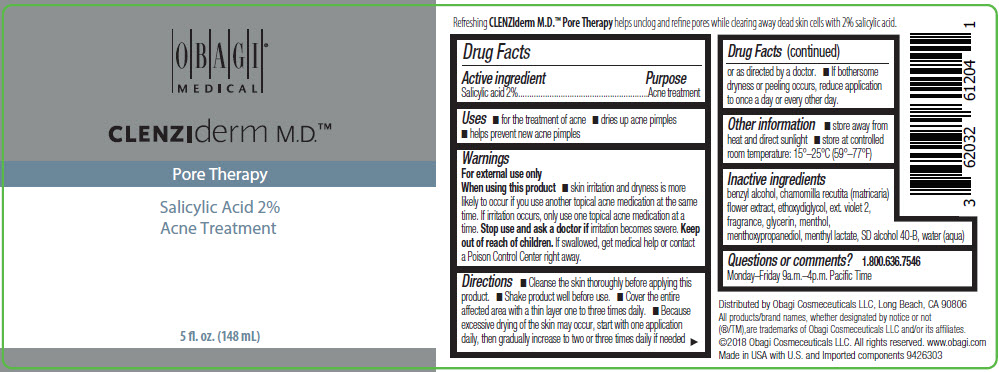 DRUG LABEL: CLENZIDERM PORE THERAPY
NDC: 62032-612 | Form: LIQUID
Manufacturer: Obagi Cosmeceuticals LLC
Category: otc | Type: HUMAN OTC DRUG LABEL
Date: 20250101

ACTIVE INGREDIENTS: SALICYLIC ACID 20 mg/1 mL
INACTIVE INGREDIENTS: ALCOHOL; DIETHYLENE GLYCOL MONOETHYL ETHER; BENZYL ALCOHOL; 3-((L-MENTHYL)OXY)PROPANE-1,2-DIOL; CHAMOMILE; GLYCERIN; MENTHOL, UNSPECIFIED FORM; MENTHYL LACTATE, (-)-; EXT. D&C VIOLET NO. 2; WATER

CLENZIDERM PORE THERAPY
ACNE TREATMENT

Drug Facts

Active ingredient

Salicylic acid 2%

Purpose

Acne treatment

Uses

- for the treatment of acne
- dries up acne pimples
- helps prevent new acne pimples

Warnings

For external use only

When using this product

- skin irritation and dryness is more likely to occur if you use another topical acne medication at the same time. If irritation occurs, only use one topical acne medication at a time.

Stop use and ask a doctor if irritation becomes severe.

Keep out of reach of children. If swallowed, get medical help or contact a Poison Control Center right away.

Directions

- Cleanse the skin thoroughly before applying this product.
- Shake product well before use.
- Cover the entire affected area with a thin layer one to three times daily.
- Because excessive drying of the skin may occur, start with one application daily, then gradually increase to two or three times daily if needed or as directed by a doctor.
- If bothersome dryness or peeling occurs, reduce application to once a day or every other day.

Other information

- store away from heat and direct sunlight
- store at controlled room temperature: 15°–25°C (59°–77°F)

Inactive ingredients

benzyl alcohol, chamomilla recutita (matricaria) flower extract, ethoxydiglycol, ext. violet 2, fragrance, glycerin, menthol, menthoxypropanediol, menthyl lactate, SD alcohol 40-B, water (aqua)

Questions or comments?

1.800.636.7546 Monday–Friday 9a.m.–4p.m. Pacific Time

Distributed by Obagi Cosmeceuticals LLC, Long Beach, CA 90806

PRINCIPAL DISPLAY PANEL - 148 mL Bottle Label

OBAGI®
MEDICAL

CLENZIderm M.D.™

Pore Therapy

Salicylic Acid 2%
Acne Treatment

5 fl. oz. (148 mL)